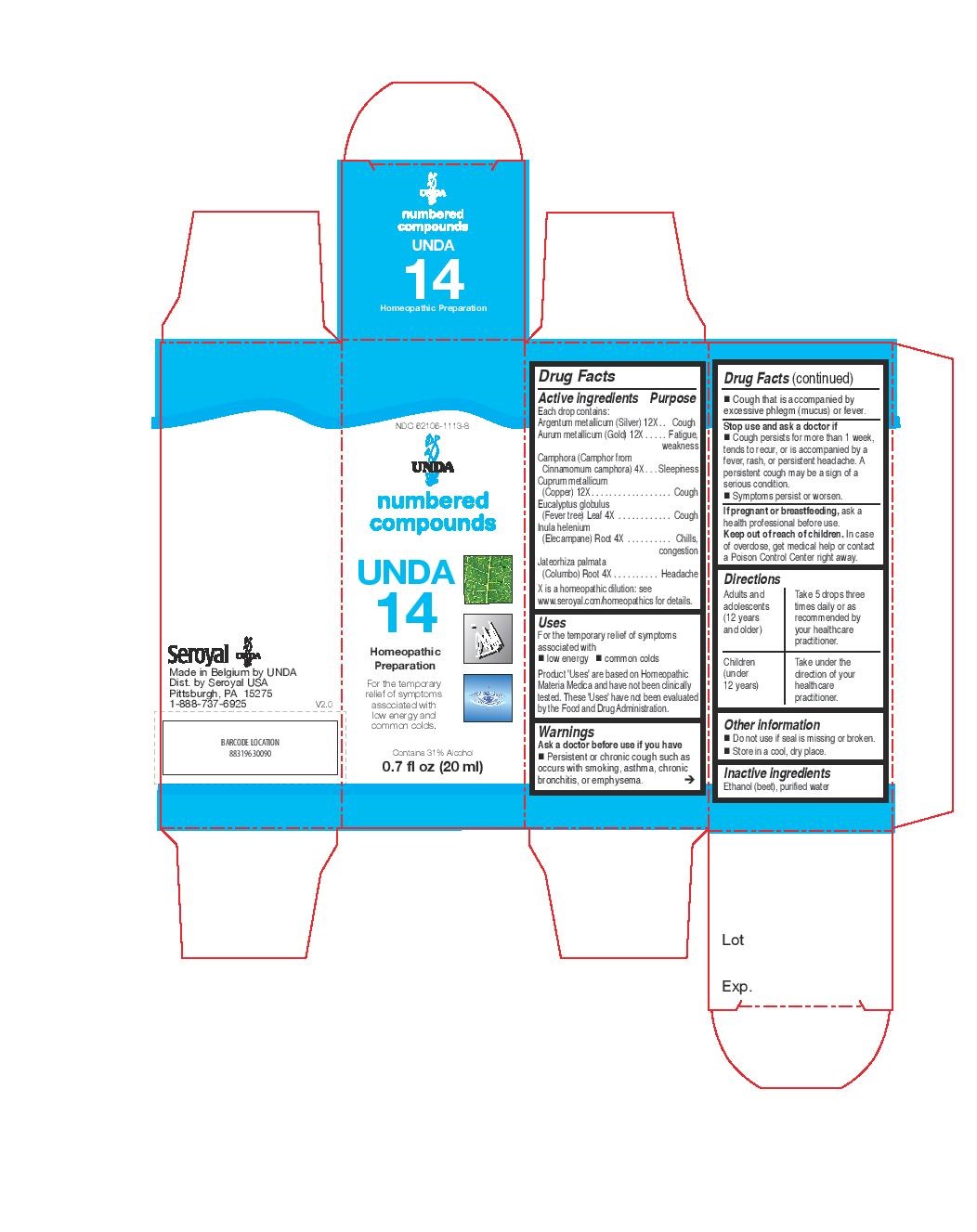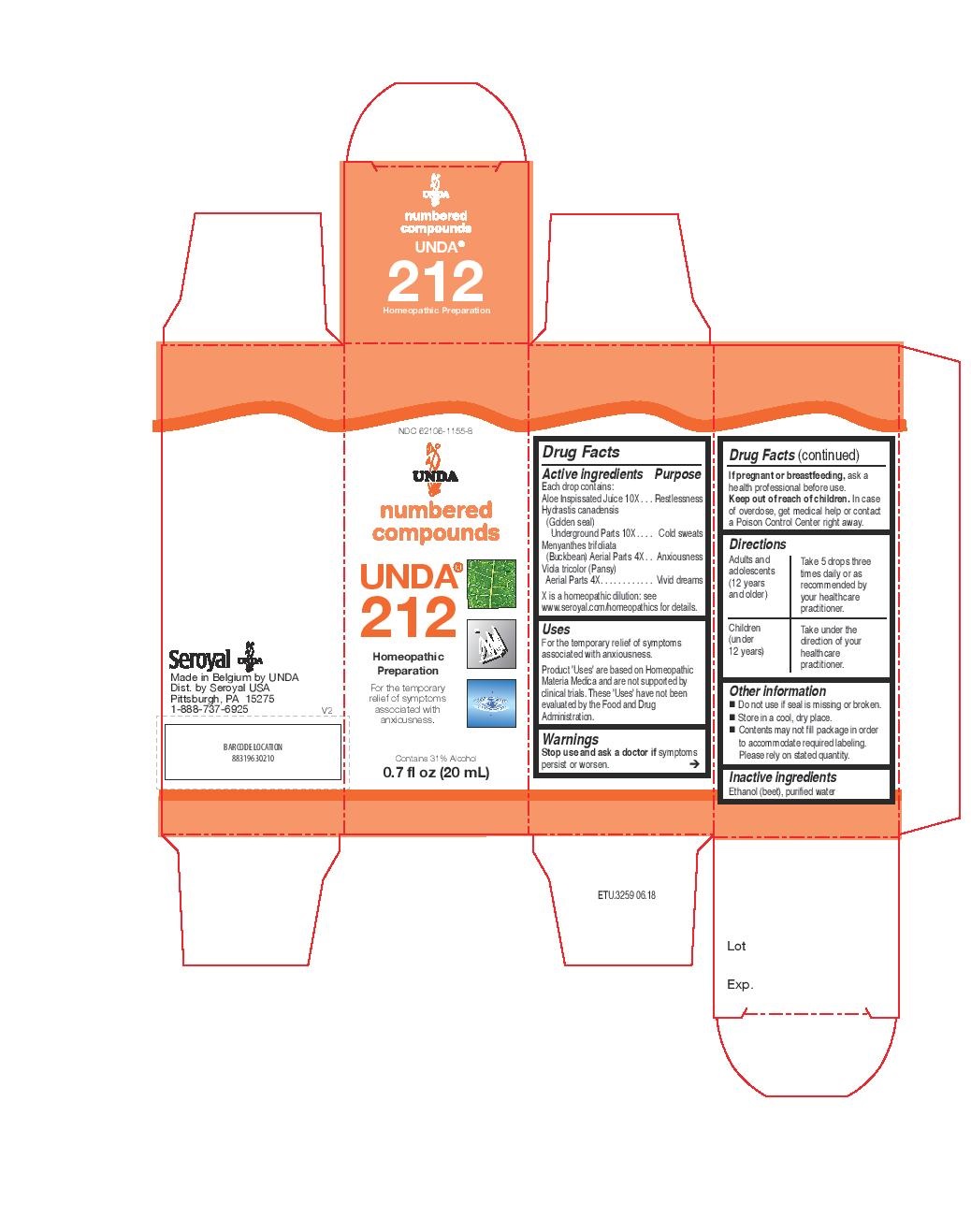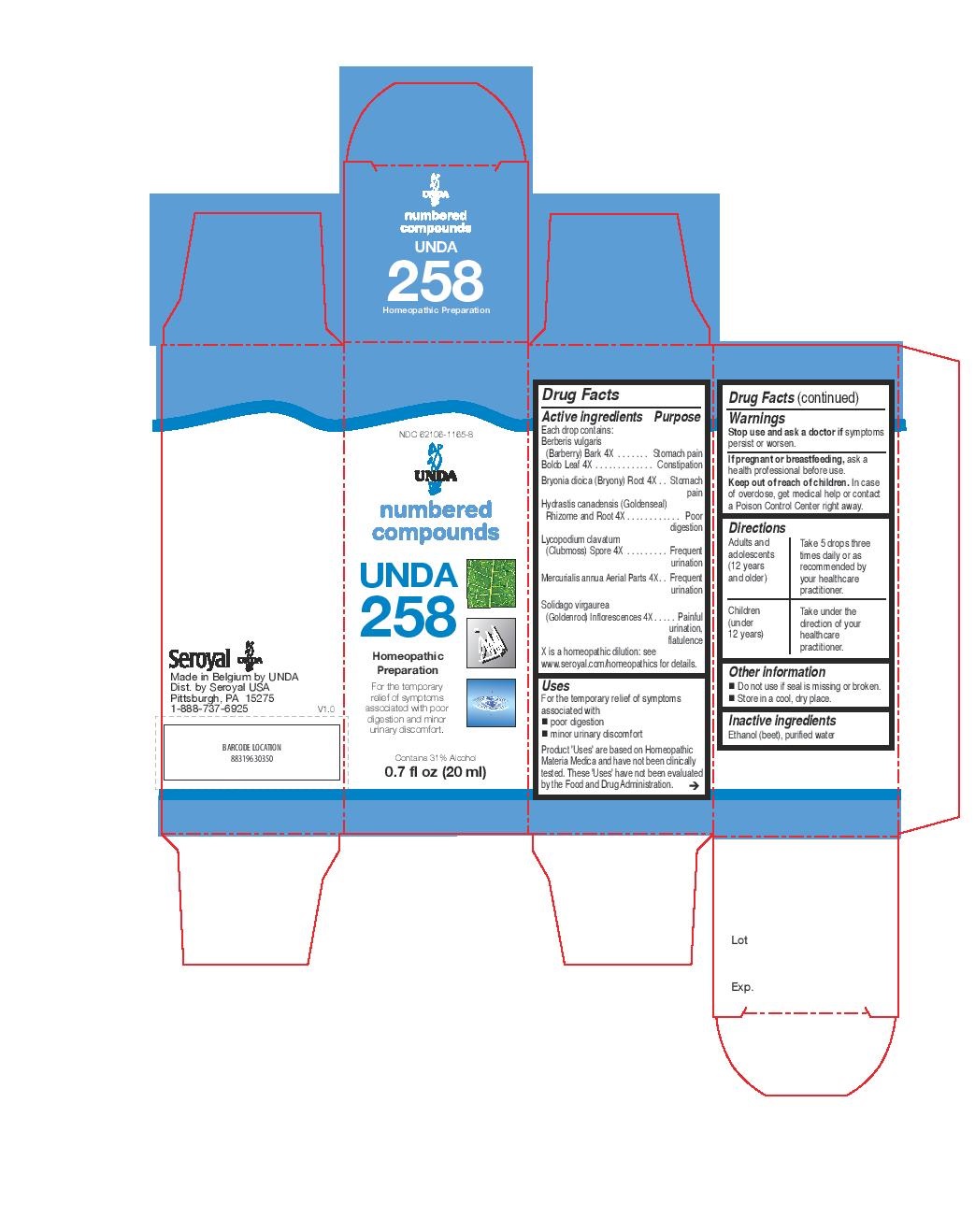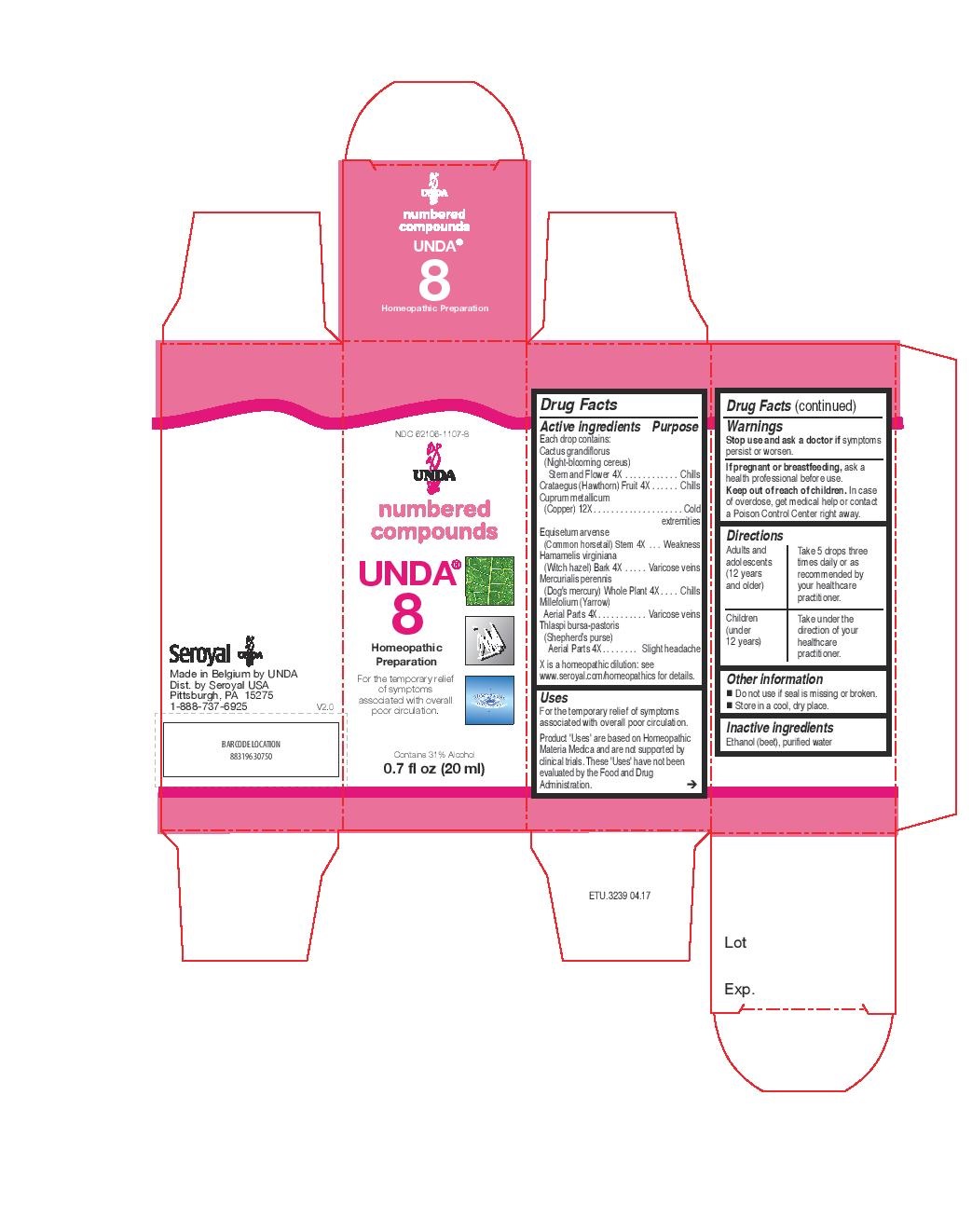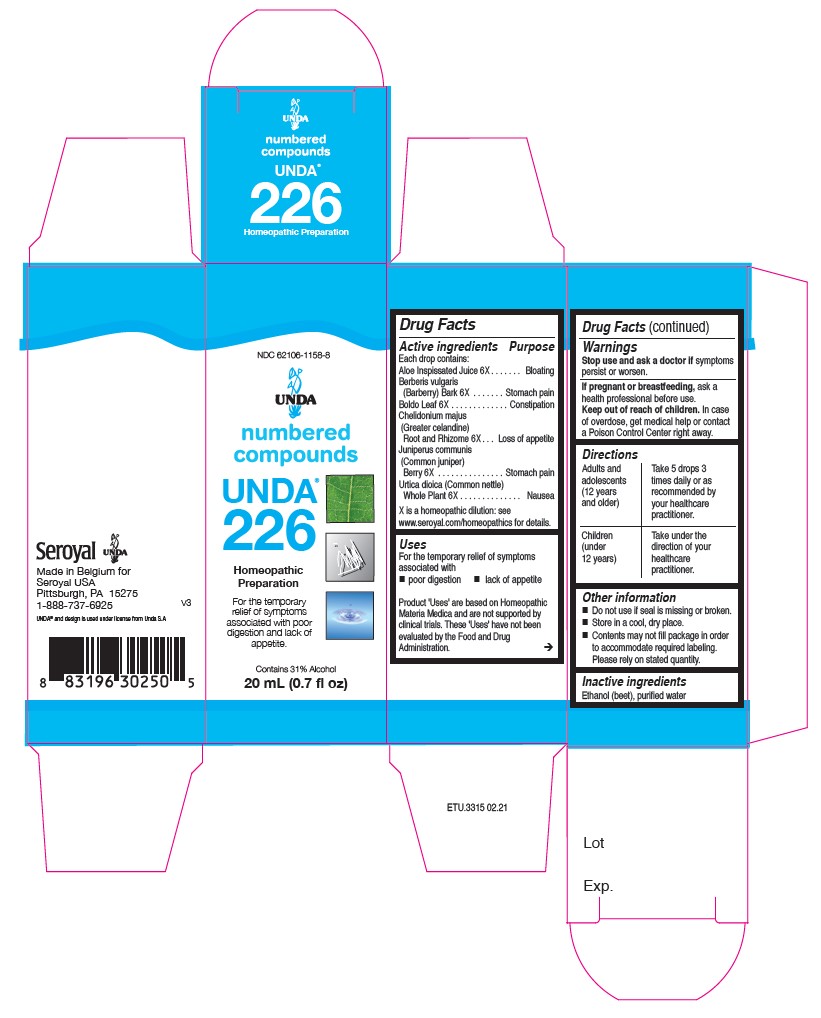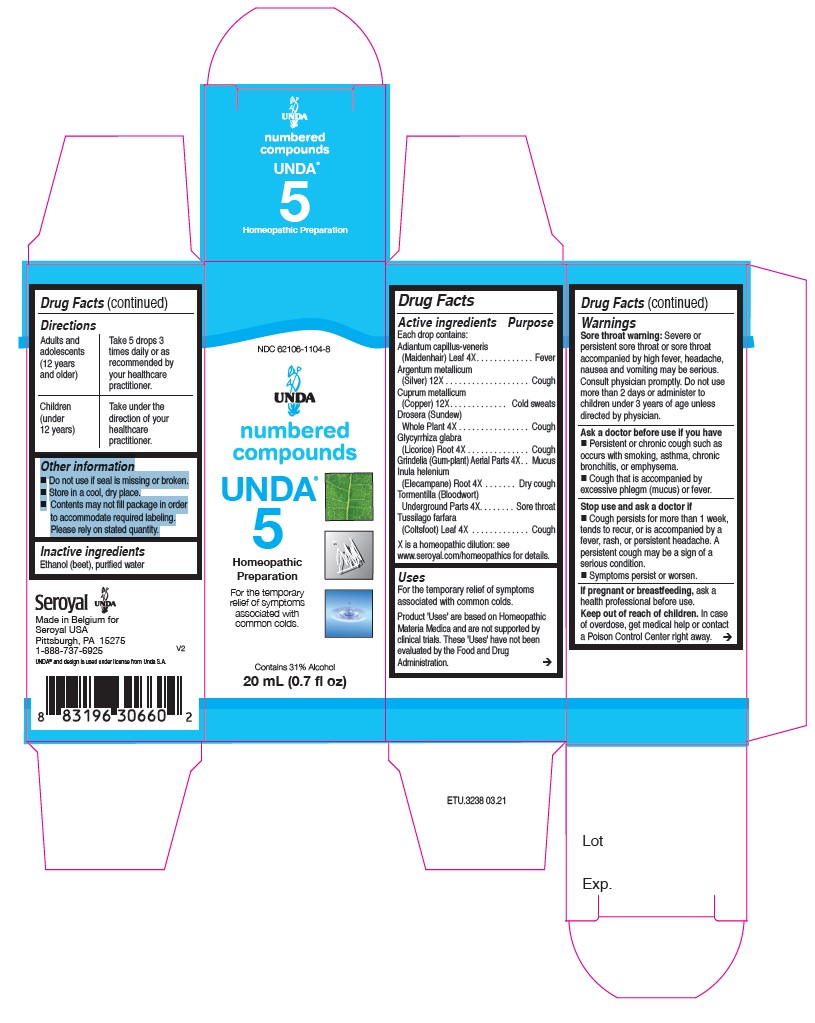 DRUG LABEL: UNDA 8
NDC: 62106-1107 | Form: LIQUID
Manufacturer: Seroyal USA
Category: homeopathic | Type: HUMAN OTC DRUG LABEL
Date: 20210715

ACTIVE INGREDIENTS: HAMAMELIS VIRGINIANA BARK 4 [hp_X]/20 mL; MERCURIALIS PERENNIS 4 [hp_X]/20 mL; CRATAEGUS FRUIT 4 [hp_X]/20 mL; COPPER 12 [hp_X]/20 mL; ACHILLEA MILLEFOLIUM 4 [hp_X]/20 mL; EQUISETUM ARVENSE BRANCH 4 [hp_X]/20 mL; CAPSELLA BURSA-PASTORIS 4 [hp_X]/20 mL; SELENICEREUS GRANDIFLORUS STEM 4 [hp_X]/20 mL
INACTIVE INGREDIENTS: ALCOHOL; WATER

Unda numbers

Active ingredients

Each drop contains:

Tormentilla (Bloodwort) Rhizome . 4X
Tussilago farfara (Coltsfoot) Whole Plant . 4X
Adiantum capillus-veneris (Maidenhair) Leaf. 4X
Glycyrrhiza glabra (Licorice) Root . 4X
Drosera (Sundew)Whole Plant . 4X
Grindelia Aerial Parts. 4X
Inula helenium (Elecampane) Root . 4X
Cuprum metallicum(Copper) . 12X
Argentum metallicum(Silver). 12X

Uses

For the temporary relief of symptoms
associated with common colds.

Warnings

Sore throat warning: Severe or persistent sore throat or sore throat accompanied by high fever, headache,
nausea and vomiting may be serious.
Consult physician promptly. Do not use more than 2 days or administer to children under 3 years of age unless directed by physician.

Ask a doctor before use if you have Persistent or chronic cough such as occurs with smoking, asthma, chronic
bronchitis, or emphysema. Cough that is accompanied by excessive phlegm (mucus) or fever.

Stop use and ask a doctor if Cough persists for more than 1 week, tends to recur, or is accompanied by a
fever, rash, or persistent headache. A persistent cough may be a sign of a serious condition.
And if symptoms persist or worsen.

If pregnant or breastfeeding, ask a health professional before use.
Keep out of reach of children.

In case of overdose, get medical help or contact a Poison Control Center right away.

PREGNANCY OR BREAST FEEDING

If you are pregnant or breastfeeding, ask a healthcare practitioner before use.

Keep out of reach of children.

OVERDOSAGE

In case of overdose, get medical help or contact a Poison Control Center right away.

Inactive Ingredients:

Ethanol (beet),
purified water

Directions

Adults and adolescents (12 years and older)

Take 5 drops three times daily or as recommended by your healthcare practitioner.

Children (under 12 years)

Take under the direction of your healthcare practitioner.

Uses

For the temporary relief of symptoms associated with common colds.

Directions

Adults and adolescents (12 years and older)

Take 5 drops three times daily or as recommended by your healthcare practitioner.

Children (under 12 years)

Take under the direction of your healthcare practitioner.

Active ingredients

Each drop contains:
Cactus grandiflorus (Night-blooming cereus) Stem and Flower 4X
Crataegus (Hawthorn) Fruit 4X
Cuprum metallicum (Copper) 12X
Equisetum arvense (Common horsetail) Stem 4X
Hamamelis virginiana (Witch hazel) Bark 4X
Mercurialis perennis (Dog's mercury) Whole Plant 4X
Millefolium (Yarrow) Aerial Parts 4X
Thlaspi bursa-pastoris (Shepherd’s purse) Aerial Parts 4X

Uses
For the temporary relief of symptoms associated with overall poor circulation.

Warnings
Stop use and ask a doctor if symptoms
persist or worsen.
If pregnant or breastfeeding, ask a
health professional before use.
Keep out of reach of children. In case
of overdose, get medical help or contact
a Poison Control Center right away.

PREGNANCY OR BREAST FEEDING

If pregnant or breastfeeding, ask a health professional before use.

Keep out of reach of children.

OVERDOSAGE

In case of overdose, get medical help or contact a Poison Control Center right away.

Stop use and ask a doctor if symptoms persist or worsen

Inactive Ingredients:

Ethanol (beet),
purified water

Directions

Adults and adolescents (12 years and older)

Take 5 drops three times daily or as recommended by your healthcare practitioner.

Children (under 12 years)

Take under the direction of your healthcare practitioner.

Uses
For the temporary relief of symptoms associated with overall poor circulation.

Directions

Adults and adolescents (12 years and older)

Take 5 drops three times daily or as recommended by your healthcare practitioner.

Children (under 12 years)

Take under the direction of your healthcare practitioner.

Other information
Do not use if seal is missing or broken.
Store in a cool, dry place.

Active ingredients
Each drop contains:
Argentum metallicum (Silver) 12X
Aurum metallicum (Gold) 12X
Camphora (Camphor from
Cinnamomum camphora) 4X
Cuprum metallicum (Copper) 12X
Eucalyptus globulus (Fever tree) Leaf 4X
Inula helenium (Elecampane) Root 4X
Jateorhiza palmata (Columbo) Root 4X

Uses
For the temporary relief of symptoms
associated with low energy and common colds

Warnings
Ask a doctor before use if you have
Persistent or chronic cough such as
occurs with smoking, asthma, chronic
bronchitis, or emphysema.

Cough that is accompanied by
excessive phlegm (mucus) or fever.
Stop use and ask a doctor if
Cough persists for more than 1 week,
tends to recur, or is accompanied by a
fever, rash, or persistent headache. A
persistent cough may be a sign of a
serious condition.
Symptoms persist or worsen.
If pregnant or breastfeeding, ask a
health professional before use.
Keep out of reach of children. In case
of overdose, get medical help or contact
a Poison Control Center right away.

PREGNANCY OR BREAST FEEDING

If you are pregnant or breastfeeding, ask a healthcare practitioner before use.

Keep out of reach of children.

OVERDOSAGE

In case of overdose, get medical help or contact a Poison Control Center right away.

Stop use and ask a doctor if
Cough persists for more than 1 week,
tends to recur, or is accompanied by a
fever, rash, or persistent headache. A
persistent cough may be a sign of a
serious condition.
Symptoms persist or worsen.

Inactive Ingredients:

Ethanol (beet),
purified water

Directions

Adults and adolescents (12 years and older): Take 5 drops three times daily or as
recommended by your healthcare practitioner.
Children (under 12 years): Take under the direction of your
healthcare practitioner.

Uses
For the temporary relief of symptoms
associated with low energy and common colds

Directions
Adults and adolescents (12 years and older): Take 5 drops three times daily or as
recommended by your healthcare practitioner.
Children (under 12 years): Take under the direction of your
healthcare practitioner.

Other information
Do not use if seal is missing or broken.
Store in a cool, dry place.

Active ingredients

Each drop contains:

Menyanthes trifoliata (Buckbean) Whole Plant . 4X
Viola tricolor (Pansy) Whole Plant. 4X
Hydrastis canadensis (Golden seal) Rhizome and Root . 10X
Aloe socotrina (Aloes) Inspissated Juice. 10X

PURPOSE

Indications
For the relief of symptoms associated with anxiousness.

Warnings
If you are pregnant or breastfeeding, ask a healthcare practitioner before use.
Keep out of reach of children.
In case of overdose, get medical help or contact a Poison Control Center right away.
If symptoms persist or worsen, consult your healthcare practitioner.

PREGNANCY OR BREAST FEEDING

If you are pregnant or breastfeeding, ask a healthcare practitioner before use.

Keep out of reach of children.

OVERDOSAGE

In case of overdose, get medical help or contact a Poison Control Center right away.

ASK DOCTOR

If symptoms persist or worsen, consult your healthcare practitioner.

Inactive Ingredients:

Ethanol (beet),
purified water

Directions

Adults and adolescents (12 years and older)

Take 5 drops three times daily or as recommended by your healthcare practitioner.

Children (under 12 years)

Take under the direction of your healthcare practitioner.

Indications
For the relief of symptoms associated with anxiousness.

Directions

Adults and adolescents (12 years and older)

Take 5 drops three times daily or as recommended by your healthcare practitioner.

Children (under 12 years)

Take under the direction of your healthcare practitioner.

Active ingredients
Each drop contains:
Aloe Inspissated Juice 6X
Berberis vulgaris (Barberry) Bark 6X
Boldo Leaf 6X
Chelidonium majus (Greater celandine) Root and Rhizome 6X
Juniperus communis (Common juniper) Berry 6X
Urtica dioica (Common nettle) Whole Plant 6X

Uses

For the temporary relief of symptoms associated with poor digestion and lack of appetite.

Warnings
Stop use and ask a doctor if symptoms
persist or worsen.

If pregnant or breastfeeding, ask a
health professional before use.
Keep out of reach of children. In case
of overdose, get medical help or contact
a Poison Control Center right away.

PREGNANCY OR BREAST FEEDING

If you are pregnant or breastfeeding, ask a healthcare practitioner before use.

Keep out of reach of children.

OVERDOSAGE

In case of overdose, get medical help or contact a Poison Control Center right away.

Stop use and ask a doctor If symptoms persist or worsen.

Inactive Ingredients:

Ethanol (beet),
purified water

Directions
Adults and adolescents (12 years and older): Take 5 drops three times daily or as
recommended by your healthcare practitioner.
Children (under 12 years): Take under the direction of your
healthcare practitioner.

Uses
For the temporary relief of symptoms associated with poor digestion and lack of appetite.

Directions
Adults and adolescents (12 years and older): Take 5 drops three times daily or as
recommended by your healthcare practitioner.
Children (under 12 years): Take under the direction of your
healthcare practitioner.

Other information
Do not use if seal is missing or broken.
Store in a cool, dry place.

Active ingredients
Each drop contains:
Berberis vulgaris (Barberry) Bark 4X
Boldo Leaf 4X
Bryonia dioica (Bryony) Root 4X
Hydrastis canadensis (Goldenseal) Rhizome and Root 4X
Lycopodium clavatum (Clubmoss) Spore 4X
Mercurialis annua Aerial Parts 4X
Solidago virgaurea (Goldenrod) Inflorescences 4X

Uses
For the temporary relief of symptoms associated with
poor digestion
minor urinary discomfort

Warnings

Stop use and ask a doctor if symptoms persist or worsen.

If you are pregnant or breastfeeding, ask a healthcare practitioner before use.
Keep out of reach of children.
In case of overdose, get medical help or contact a Poison Control Center right away.

PREGNANCY OR BREAST FEEDING

If you are pregnant or breastfeeding, ask a healthcare practitioner before use.

Keep out of reach of children.

OVERDOSAGE

In case of overdose, get medical help or contact a Poison Control Center right away.

Inactive Ingredients:

Ethanol (beet),
purified water

Directions
Adults and adolescents (12 years and older)

Take 5 drops three times daily or as recommended by your healthcare practitioner.

Children (under 12 years)

Take under the direction of your healthcare practitioner.

Uses
For the temporary relief of symptoms associated with
poor digestion
minor urinary discomfort

Directions
Adults and adolescents (12 years and older)

Take 5 drops three times daily or as recommended by your healthcare practitioner.

Children (under 12 years)

Take under the direction of your healthcare practitioner.

Other information
Do not use if seal is missing or broken.
Store in a cool, dry place.
Contents may not fill package in order
to accommodate required labeling.
Please rely on stated quantity.

PACKAGE LABEL

NDC 62106-1165-8

UNDA

numbered compounds

UNDA 258

Homeopathic Preparation

For the temporary relief of symptoms associated with poor digestion and minor urinary discomfort.

Contains 31% Alcohol
0.7 fl oz (20 ml)

PACKAGE LABEL

NDC 62106-1107-8

UNDA

numbered compounds

UNDA 8

Homeopathic Preparation

For the temporary relief of symptoms
associated with overall poor circulation.

Contains 31% Alcohol
0.7 fl oz (20 ml)

PACKAGE LABEL

NDC 62106-1113-8

UNDA

numbered compounds

UNDA 14

Homeopathic Preparation

For the temporary
relief of symptoms
associated with
low energy and
common colds.

Contains 31% Alcohol
0.7 fl oz (20 ml)

PACKAGE LABEL

NDC 62106-1158-8

UNDA

numbered compounds

UNDA 226

Homeopathic Preparation

For the temporary relief of symptoms associated

with poor digestion and lack of appetite.

Contains 31% Alcohol

0.7 fl oz (20 ml)

PACKAGE LABEL

UNDA

numbered compounds

NDC 62106-1104-8

UNDA 5

Homeopathic Preparation

For the temporary relief of symptoms associated with common colds.

Contains 31% Alcohol
0.7 fl oz (20 ml)

PACKAGE LABEL

NDC 62106-1155-8

UNDA

numbered compounds

UNDA 212

Homeopathic Preparation

For the temporary relief of symptoms associated with anxiousness.

Contains 31% Alcohol

0.7 fl oz (20 mL)